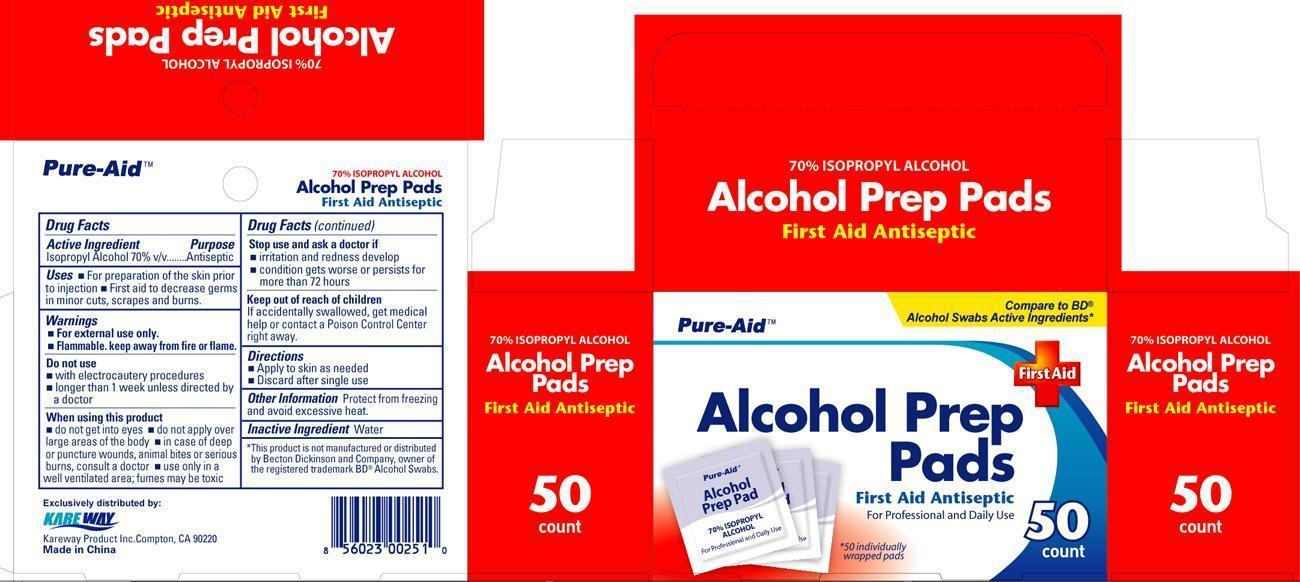 DRUG LABEL: Alcohol Prep Pads
NDC: 67510-0251 | Form: SWAB
Manufacturer: Kareway Product, Inc.
Category: otc | Type: HUMAN OTC DRUG LABEL
Date: 20201005

ACTIVE INGREDIENTS: ISOPROPYL ALCOHOL 70 1/1 1
INACTIVE INGREDIENTS: WATER

Pure-Aid Alcohol Prep Pads

Active Ingredient

Isopropyl Alcohol 70%

Purpose

Antiseptic

Uses

- For preparation of the skin prior to injection
- First aid to decrease germs in minor cuts, scrapes and burns

Warnings

- For external use only.
- Flammable, keep away from fire or flame.

Do not use

- with electrocautery procedures
- longer than 1 week unless directed by a doctor

When using this product

- do not get into eyes
- do not apply over large areas of the body
- in case of deep or puncture wounds, animal bites or serious burns, consult a doctor
- use only in a well ventilated area:fumes may be toxic

Stop use and ask a doctor if

- irritation and redness develop
- condition gets worse or persists for more than 72 hours

Keep out of reach of children

If accidentally swallowed, get medical help or contact a Poison Control Center righ away.

Directions

- Apply to skin as needed
- Discard after single use

Other Information

Protect from freezing and avoid excessive heat.

Inactive Ingredient

Water

PACKAGE LABEL

Alcohol Prep Pads 50ct